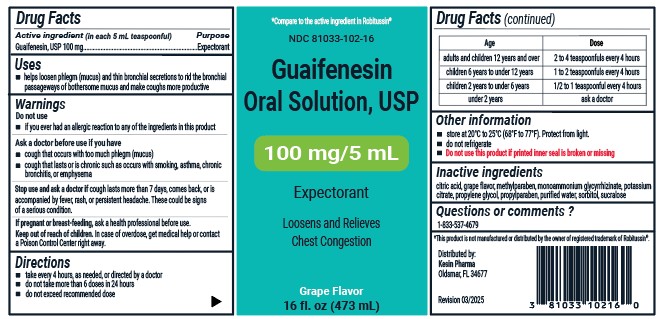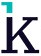 DRUG LABEL: Guaifenesin
NDC: 81033-102 | Form: LIQUID
Manufacturer: KESIN PHARMA CORPORATION
Category: otc | Type: HUMAN OTC DRUG LABEL
Date: 20250401

ACTIVE INGREDIENTS: GUAIFENESIN 100 mg/5 mL
INACTIVE INGREDIENTS: POTASSIUM CITRATE ANHYDROUS; METHYLPARABEN; AMMONIUM GLYCYRRHIZATE; SORBITOL; CITRIC ACID; SUCRALOSE; PROPYLPARABEN; WATER; PROPYLENE GLYCOL

Guaifenesin Oral Solution, USP

Drug Facts

Active ingredient (in each 5 mL teaspoonful)

Guaifenesin, USP 100 mg

Purpose

Expectorant

Uses

- helps loosen phlegm (mucus) and thin bronchial secretions to rid the bronchial passageways of bothersome mucus and make coughs more productive

Warnings

Do not use

- if you ever had an allergic reaction to any of the ingredients in this product

Ask a doctor before use if you have

- cough that occurs with too much phlegm (mucus)
- cough that lasts or is chronic such as occurs with smoking, asthma, chronic, bronchitis, emphysema

Stop use and ask a doctor if

cough lasts more than 7 days, comes back, or is accompanied by fever, rash, or persistant headache. These could be signs of a serious condition.

If pregnant or breast-feeding,

ask a health professional before use.

OVERDOSAGE

In case of overdose, get medical help or contact a Poison Control Center right away.

Directions

- take every 4 hours, as needed, or directed by a doctor
- do not take more than 6 doses in 24 hours
- do not exceed recommended dose

Age | Dose
adults and children 12 years and over | 2 to 4 tespoonfuls every 4 hours
children 6 years to under 12 years | 1 to 2 teaspoonfuls every 4 hours
children 2 years to under 6 years | 1/2 to 1 teaspoonful every 4 hours
under 2 years | ask a doctor

Other information

- store at 20ºC to 25ºC (68ºF to 77ºF). Protect from light.
- do not refrigerate
- Do not use this product of printed inner seal is broken or missing

Inactive ingredients

citric acid, grape flavor, methylparaben, monoammonium glycyrrhizinate, potassium citrate, propylene glycol, propylparaben, purified water, sorbitol, sucralose

Questions or comments?

1-833-537-4679

*This product is not manufactured or distributed by the owner of registered trademark of Robitussin®.

Distributed by:

Kesin Pharma

Oldsmar, FL 34677

Revision 03/2025

PACKAGE LABEL

NDC 81033-102-16

Guaifenesin Oral Solution, USP

100 mg/5 mL

Expectorant

Grape Flavor

16 fl oz (473 mL)